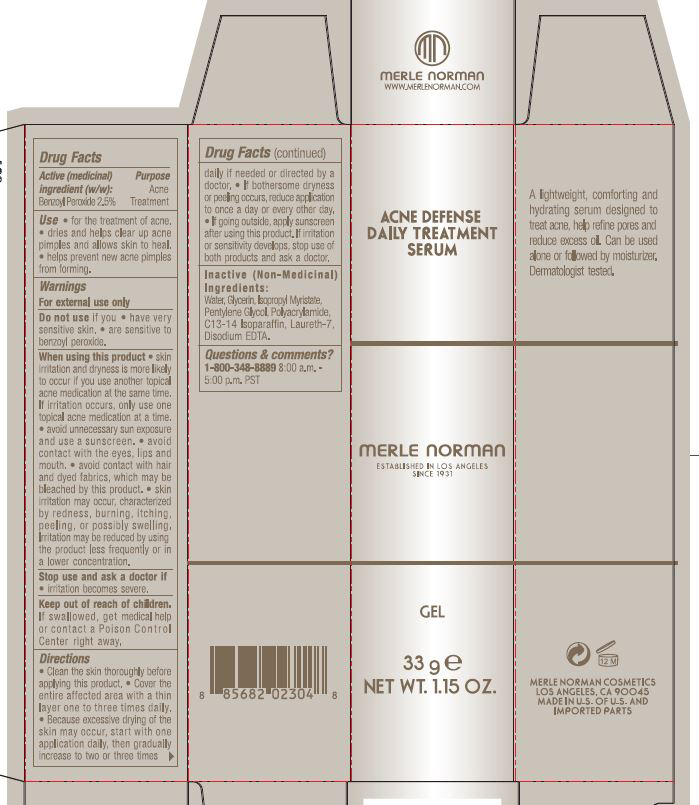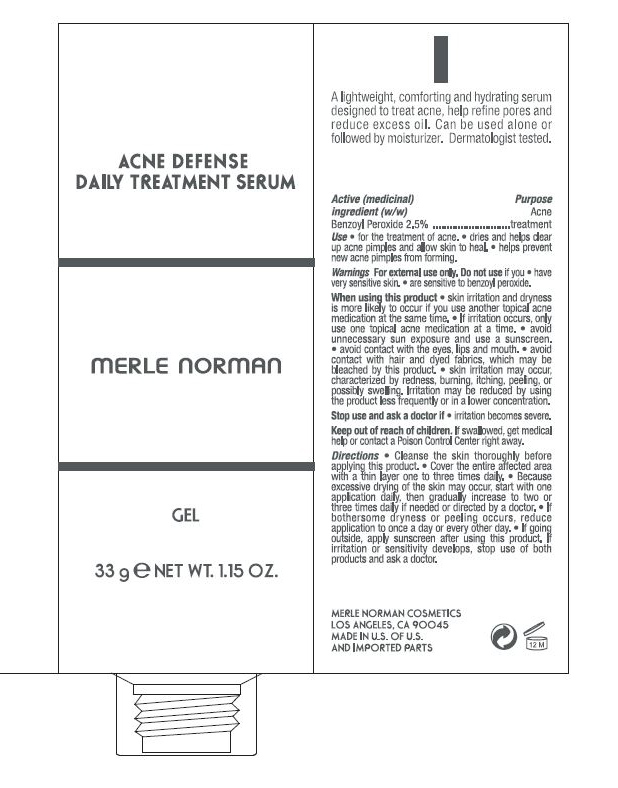 DRUG LABEL: Acne defense Daily Treatment Serum
NDC: 57627-202 | Form: GEL
Manufacturer: Merle Norman Cosmetics
Category: otc | Type: HUMAN OTC DRUG LABEL
Date: 20200127

ACTIVE INGREDIENTS: BENZOYL PEROXIDE 2.5 g/100 g
INACTIVE INGREDIENTS: WATER; ISOPROPYL MYRISTATE; PENTYLENE GLYCOL; POLYACRYLAMIDE (1500 MW); C13-14 ISOPARAFFIN; LAURETH-7; EDETATE DISODIUM

Acne Defense Daily Treatment Serum

Active (medicinal) Purpose

Benzoyl Peroxide 2.5% Acne Treatment

Uses

For the treatment of acne

Dries and helps clear up acne pimples and allows skin to heal

helps prevent new acne pimples from forming

Keep out of reach of children. If swallowed, get medical help or contact a Poison Control Center right away

Stop use and ask a doctor if

- irritation becomes severe

Warnings

For external use only

Do not use if

- have very senstive skin
- are sensitive to benzoyl peroxide

When using this product

skin irritation and dryness is more likely to occur if you use another topical acne medication at the same time. If irritation occurs only use one topical acne medication at a time.

Avoid unnecessary sun exposure and use a sunscreen

avoid contact with eyes, lips and mouth

avoid contact with hair and dyed fabrics which may be bleached by this product

Skin irritation may occur, characterized by redness, burning, itching, peeling or possibly swelling. Irriration may be reduced by using the product less frequently or in a lower concentration

Directions

- Clean the skin thoroughly before applying this product

- Cover the entire affected area with a thin layer one to three times daily

- Because excessive drying of the skin may occur, start with one application daily then gradually increase to two or three times daily if needed or directed by a doctor. If bothersome dryness or peeing occurs, reduce application to once a day or every other day

- If going outside apply sunscreen after using this product. If irritation or sensitivity develops, stop use of both products and ask a doctor

Inactive (Non-medicinal) Ingredients

Water, Glycerin, Isopropyl Myristate, Pentylene Glycol, Polyacrylamide, C13-14 Isoparrafin, Laureth-7, Disodium EDTA

PACKAGE LABEL

Acne Defense Daily Treatment Serum

Gel

33g

Net Wt. 1.15 Oz